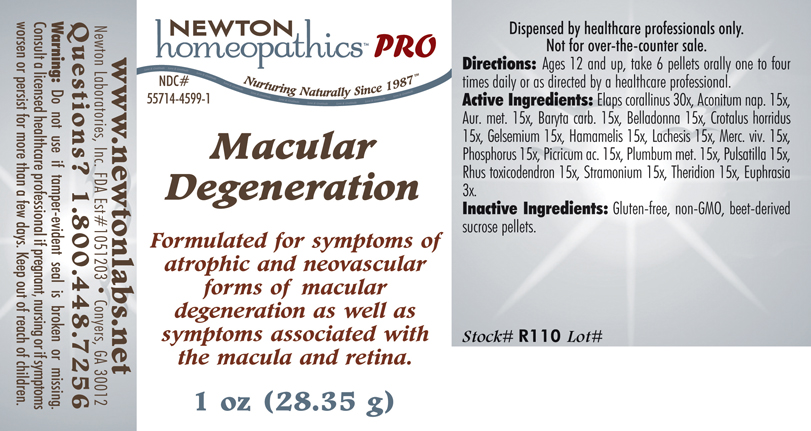 DRUG LABEL: Macular Degeneration 
NDC: 55714-4599 | Form: PELLET
Manufacturer: Newton Laboratories, Inc.
Category: homeopathic | Type: HUMAN PRESCRIPTION DRUG LABEL
Date: 20110601

ACTIVE INGREDIENTS: Micrurus Corallinus Venom 30 [hp_X]/1 g; Aconitum Napellus 15 [hp_X]/1 g; Gold 15 [hp_X]/1 g; Barium Carbonate 15 [hp_X]/1 g; Atropa Belladonna 15 [hp_X]/1 g; Crotalus Horridus Horridus Venom 15 [hp_X]/1 g; Gelsemium Sempervirens Root 15 [hp_X]/1 g; Hamamelis Virginiana Root Bark/stem Bark 15 [hp_X]/1 g; Lachesis Muta Venom 15 [hp_X]/1 g; Mercury 15 [hp_X]/1 g; Phosphorus 15 [hp_X]/1 g; Picric Acid 15 [hp_X]/1 g; Lead 15 [hp_X]/1 g; Pulsatilla Vulgaris 15 [hp_X]/1 g; Toxicodendron Pubescens Leaf 15 [hp_X]/1 g; Datura Stramonium 15 [hp_X]/1 g; Theridion Curassavicum 15 [hp_X]/1 g; Euphrasia Stricta 3 [hp_X]/1 g
INACTIVE INGREDIENTS: Sucrose

Macular Degeneration

INDICATIONS & USAGE SECTION

Macular Degeneration Formulated for symptoms of atrophic and neovascular forms of macular degeneration as well as symptoms associated with the macula and retina.

DOSAGE & ADMINISTRATION SECTION

Directions: Ages 12 and up, take 6 pellets orally one to four times daily or as directed by a healthcare professional.

ACTIVE INGREDIENT SECTION

Elaps corallinus 30x, Aconitum nap. 15x, Aur. met. 15x, Baryta carb. 15x, Belladonna 15x, Crotalus horridus 15x, Gelsemium 15x, Hamamelis 15x, Lachesis 15x, Merc. viv. 15x, Phosphorus 15x, Picricum ac. 15x, Plumbum met. 15x, Pulsatilla 15x, Rhus toxicodendron 15x, Stramonium 15x, Theridion 15x, Euphrasia 3x.

PURPOSE SECTION

Formulated for symptoms of atrophic and neovascular forms of macular degeneration as well as symptoms associated with the macula and retina.

INACTIVE INGREDIENT SECTION

Inactive Ingredients: Gluten-free, non-GMO, beet-derived sucrose pellets.

QUESTIONS? SECTION

www.newtonlabs.net Newton Laboratories, Inc. FDA Est # 1051203 - Conyers, GA 30012
Questions? 1.800.448.7256

WARNINGS SECTION

Warning: Do not use if tamper - evident seal is broken or missing. Consult a licensed healthcare professional if pregnant, nursing or if symptoms worsen or persist for more than a few days. Keep out of reach of children.

PREGNANCY OR BREAST FEEDING SECTION

Consult a licensed healthcare professional if pregnant, nursing or if symptoms worsen or persist for more than a few days.

KEEP OUT OF REACH OF CHILDREN SECTION

Keep out of reach of children.